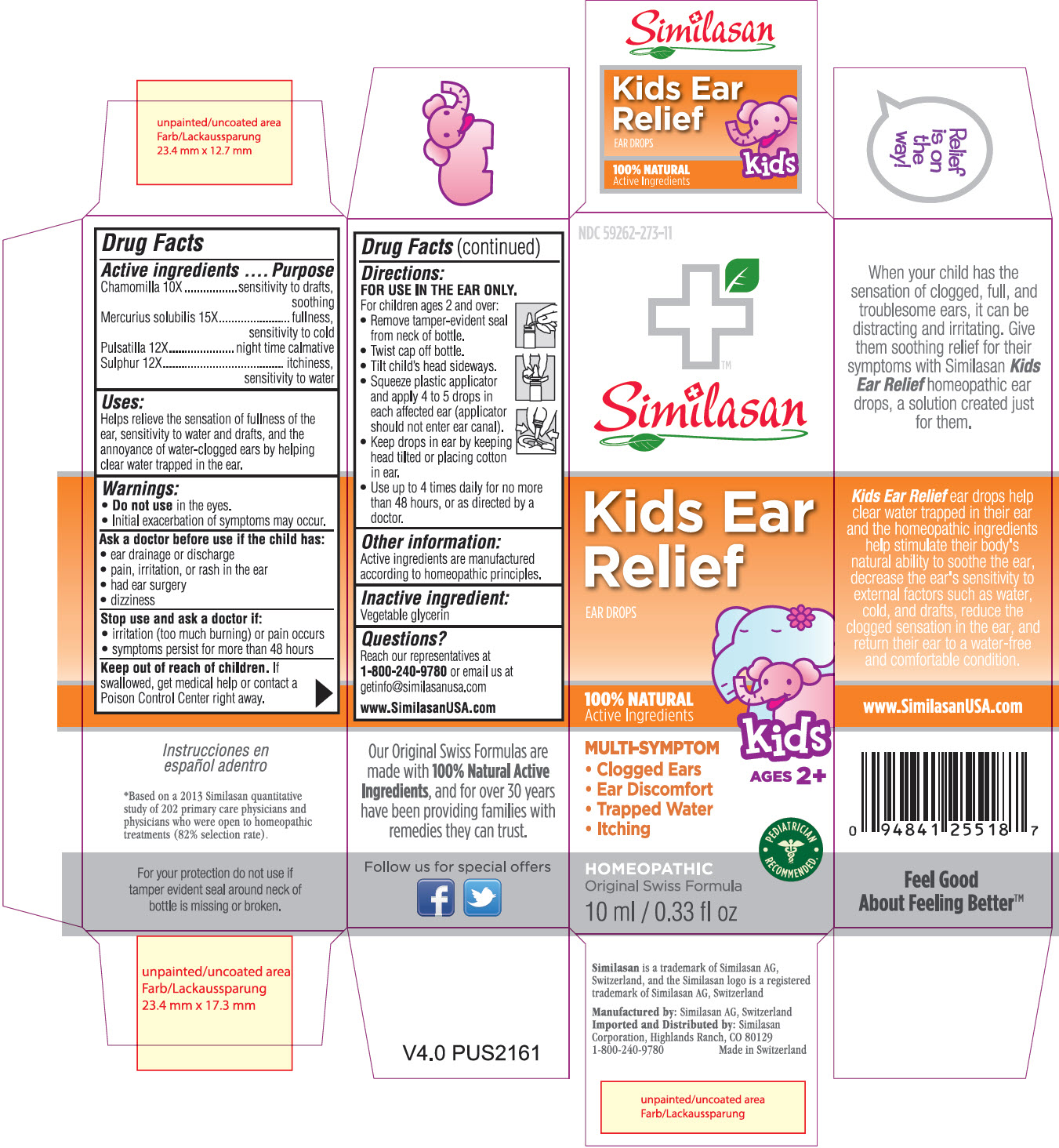 DRUG LABEL: Kids Ear Relief
NDC: 59262-273 | Form: SOLUTION
Manufacturer: Similasan Corporation
Category: homeopathic | Type: HUMAN OTC DRUG LABEL
Date: 20140129

ACTIVE INGREDIENTS: MATRICARIA RECUTITA 10 [hp_X]/10 mL; MERCURIUS SOLUBILIS 15 [hp_X]/10 mL; ANEMONE PATENS 12 [hp_X]/10 mL; SULFUR 12 [hp_X]/10 mL
INACTIVE INGREDIENTS: GLYCERIN

Kids Ear Relief

Active ingredient

Chamomilla 10X

Purpose

sensitivity to drafts, soothing

Active ingredient

Mercurius solubilis 15X

Purpose

fullness, sensitivity to cold

Active ingredient

Pulsatilla 12X

Purpose

night time calmative

Active ingredient

Sulphur 12X

Purpose

itchiness, sensitivity to water

Uses:

Helps relieve the sensation of fullness of the ear, sensitivity to water and drafts, and the annoyance of water-clogged ears by helping clear water trapped in the ear.

Warnings:

- Do not use in the eyes.
- Initial exacerbation of symptoms may occur.

Ask a doctor before use if the child has:

- ear drainage or discharge
- pain, irritation, or rash in the ear
- had ear surgery
- dizziness

Stop use and ask a doctor if:

- irritation (too much burning) or pain occurs
- symptoms persist for more than 48 hours

Keep out of reach of children.

If swallowed, get medical help or contact a Poison Control Center right away.

Directions:

FOR USE IN THE EAR ONLY.

For children ages 2 and over:

- Remove tamper-evident seal from neck of bottle.
- Twist cap off bottle.
- Tilt child’s head sideways.
- Squeeze plastic applicator and apply 4 to 5 drops in each affected ear (applicator should not enter ear canal).
- Keep drops in ear by keeping head tilted or placing cotton in ear.
- Use up to 4 times daily for no more than 48 hours, or as directed by a doctor.

Other information:

Active ingredients are manufactured according to homeopathic principles.

Inactive ingredient:

Vegetable glycerin

Questions?

Reach our representatives at 1-800-240-9780 or email us at getinfo@similasanusa.com
www.SimilasanUSA.com

PRINCIPAL DISPLAY PANEL

NDC 59262-273-11
Similasan
Kids Ear Relief
EAR DROPS
10 ml / 0.33 fl oz